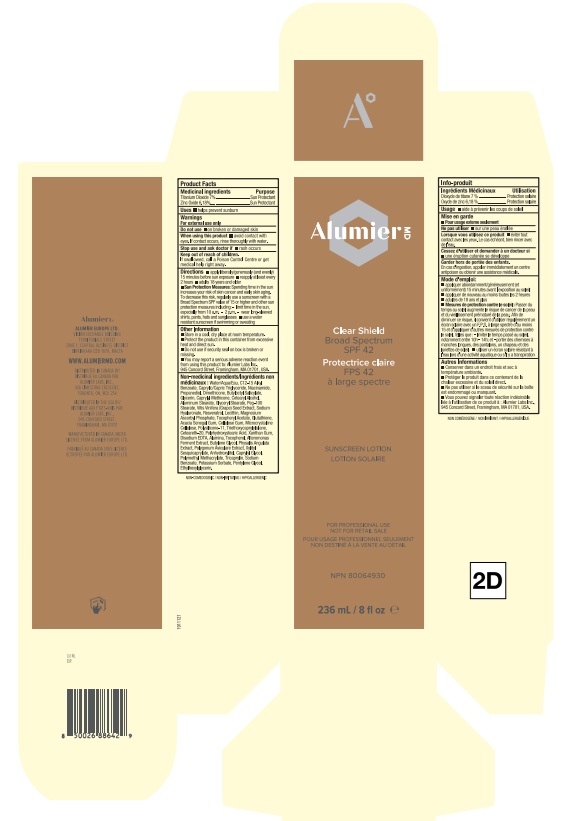 DRUG LABEL: Alumier MD Clear Shield Broad Spectrum SPF 42 Sunscreen
NDC: 69473-011 | Form: LOTION
Manufacturer: Alumier Labs
Category: otc | Type: HUMAN OTC DRUG LABEL
Date: 20260209

ACTIVE INGREDIENTS: ZINC OXIDE 61.8 mg/1 mL; TITANIUM DIOXIDE 70 mg/1 mL
INACTIVE INGREDIENTS: PHYSALIS ANGULATA; SODIUM BENZOATE; POTASSIUM SORBATE; MEDIUM-CHAIN TRIGLYCERIDES; NIACINAMIDE; DIMETHICONE/VINYL DIMETHICONE CROSSPOLYMER (SOFT PARTICLE); ALUMINUM MONOSTEARATE; TRIETHOXYCAPRYLYLSILANE; WATER; CETOSTEARYL ALCOHOL; GLYCERYL MONOSTEARATE; PEG-100 STEARATE; ACACIA; ALUMINUM OXIDE; XANTHAN GUM; CETEARETH-20; ALKYL (C12-15) BENZOATE; PROPANEDIOL; GLUTATHIONE; MAGNESIUM ASCORBYL PHOSPHATE; MICROCRYSTALLINE CELLULOSE; BUTYLENE GLYCOL; LECITHIN, SOYBEAN; EDETATE DISODIUM; XYLITYL SESQUICAPRYLATE; BUTYLOCTYL SALICYLATE; GLYCERIN; VITIS VINIFERA SEED; POLYHYDROXYSTEARIC ACID (2300 MW); RESVERATROL; .ALPHA.-TOCOPHEROL ACETATE; DIMETHICONE; HYALURONATE SODIUM; CARBOXYMETHYLCELLULOSE SODIUM, UNSPECIFIED FORM; PENTYLENE GLYCOL; TOCOPHEROL; ANHYDROXYLITOL; CAPRYLYL GLYCOL; TRICAPRYLIN; ETHYLHEXYLGLYCERIN; CAPRYLYL METHICONE; POLYGONUM AVICULARE TOP; POLY(METHYL METHACRYLATE; 450000 MW)

Alumier MD Clear Shield Sunscreen

Product Facts

Product Facts enclosed

Medicinal Ingredients

Titanium Dioxide 7%

Zinc Oxide 6.18%

Purpose

Sun Protectant

Uses

- helps prevent sunburn

Warnings

- For external use only.

Do not use

- on broken or damaged skin

When using this product

- avoid contact with eyes. If contact occurs, rinse thoroughly with water.

Stop use and ask a doctor if

- rash occurs

Keep out of reach of children.

If swallowed, call a Poison Control Centre or get medical help right away.

Directions

- apply liberally/generously (and evenly) 15 minutes before sun exposure
- reapply at least every 2 hours
- adults 18 years and older
- Sun Protection Measures: Spending time in the sun increases your risk of skin cancer and early skin aging. To decrease this risk, regularly use a sunscreen with a Broad Spectrum SPF value of 15 or higher and other sun protection measures including: - limit time in the sun, especially from 10 a.m.-2 p.m. - wear long-sleeved shirts, pants, hats and sunglasses
- use a water resistant sunscreen if swimming or sweating

Other Information

- Store in a cool, dry place at room temperature.
- Protect the product in this container from excessive heat and direct sun.
- Do not use if security seal is broken or missing.
- You may report a serious adverse reaction event from using this product to: Alumier Labs Inc., 945 Concord Street, Framingham, MA 01701, USA

Non-medicinal ingredients

Water/Aqua/Eau, C12-15 Alkyl Benzoate, Caprylic/Capric Triglyceride, Niacinamide, Propanediol, Dimethicone, Butyloctyl Salicylate, Glycerin, Caprylyl Methicone, Cetearyl Alcohol, Aluminium Stearate, Glyceryl Stearate, Peg-100 Stearate, Vitis Vinifera (Grape) Seed Extract, Sodium Hyaluronate, Resveratrol, Lecithin, Magnesium Ascorbyl Phosphate, Tocopheryl Acetate, Glutathione, Acacia Senegal Gum, Cellulose Gum, Microcrystalline Cellulose, Polysilicone-11, Triethoxycaprylylsilane, Ceteareth-20, Polyhydroxystearic Acid, Xanthan Gum, Disodium EDTA, Alumina, Tocopherol, Alteromonas Ferment Extract, Butylene Glycol, Physalis Angulata Extract, Polygonum Aviculare Extract, Xylityl Sesquicaprylate, Anhydroxyxlitol, Caprylyl Glycol, Polymethyl Methacrylate, Tricaprylin, Sodium Benzoate, Potassium Sorbate, Pentylene Glycol, Ethylhexylglycerin.